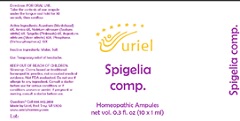 DRUG LABEL: Spigelia comp
NDC: 48951-8368 | Form: LIQUID
Manufacturer: Uriel Pharmacy Inc.
Category: homeopathic | Type: HUMAN OTC DRUG LABEL
Date: 20201216

ACTIVE INGREDIENTS: ACONITUM NAPELLUS 8 [hp_X]/1 mL; SODIUM NITRITE 8 [hp_X]/1 mL; ARNICA MONTANA FLOWER 8 [hp_X]/1 mL; PHOSPHORUS 12 [hp_X]/1 mL; SPIGELIA MARILANDICA ROOT 8 [hp_X]/1 mL; SILVER NITRATE 10 [hp_X]/1 mL
INACTIVE INGREDIENTS: SODIUM CHLORIDE; WATER

Spigelia comp

INDICATIONS AND USAGE

Directions: FOR ORAL USE.

DOSAGE AND ADMINISTRATION

Take the contents of one ampule under the tongue and hold for 30 seconds, then swallow.

ACTIVE INGREDIENT

Active Ingredients: Aconitum (Monkshood) 8X, Arnica 8X, Natrium nitrosum (Sodium nitrite) 8X, Spigelia (Pinkroots) 8X, Argentum nitricum (Silver nitrate) 10X, Phosphorus (Yellow phosphorus) 12X

Inactive Ingredients: Water, Salt

PURPOSE

Use: Temporary relief of headache.

KEEP OUT OF REACH OF CHILDREN.

WARNINGS

Warnings: Claims based on traditional homeopathic practice, not accepted medical evidence. Not FDA evaluated. Do not use if allergic to any ingredient. Consult a doctor before use for serious conditions or if conditions worsen or persist. If pregnant or nursing, consult a doctor before use.

Questions? Call 866.642.2858
Made by Uriel, East Troy, WI 53120
www.urielpharmacy.com Lot: